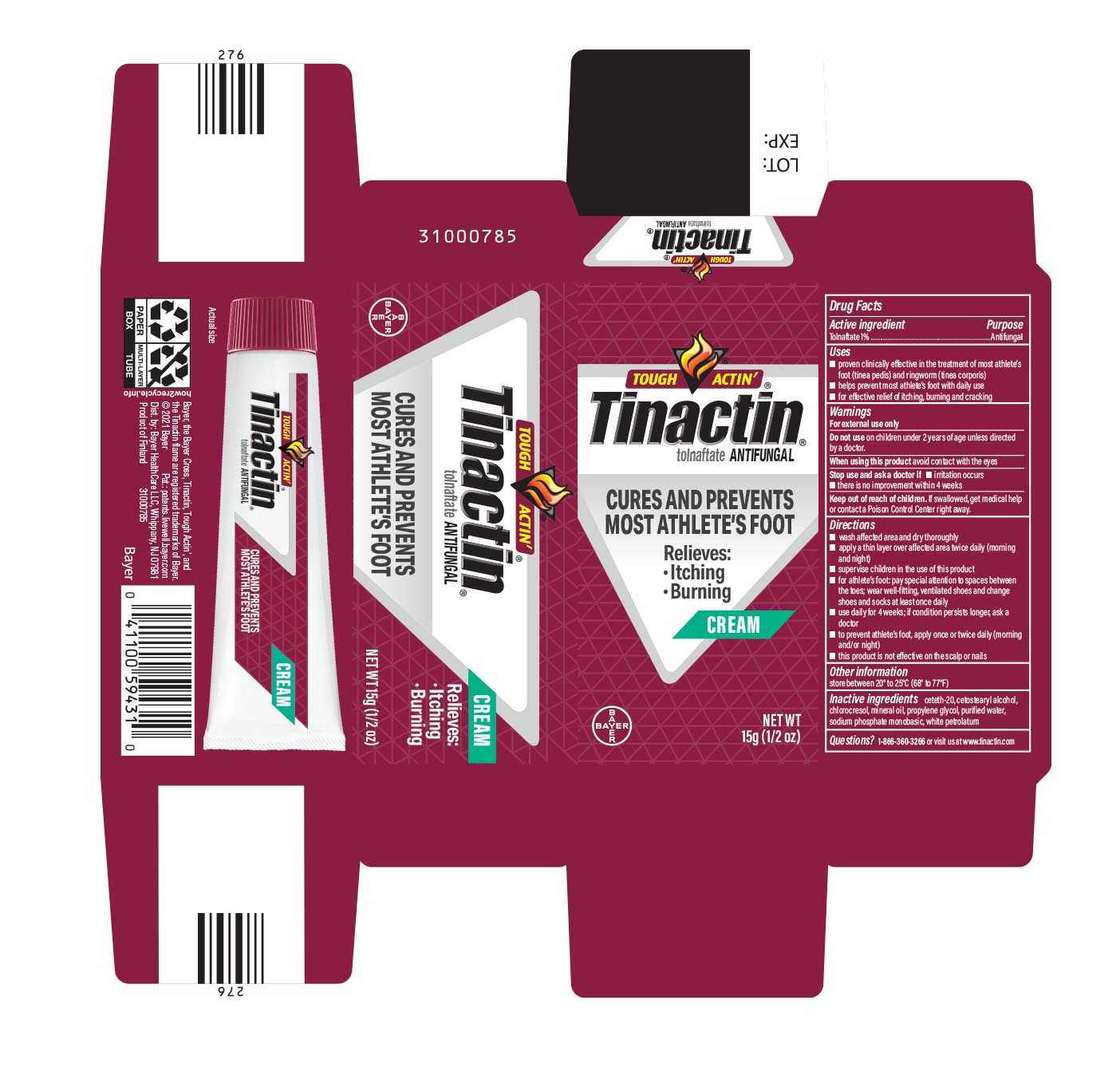 DRUG LABEL: Tinactin
NDC: 11523-1190 | Form: CREAM
Manufacturer: Bayer HealthCare LLC.
Category: otc | Type: HUMAN OTC DRUG LABEL
Date: 20251205

ACTIVE INGREDIENTS: TOLNAFTATE 10 mg/1 g
INACTIVE INGREDIENTS: CETETH-20; CETOSTEARYL ALCOHOL; CHLOROCRESOL; MINERAL OIL; PROPYLENE GLYCOL; WATER; SODIUM PHOSPHATE, MONOBASIC; PETROLATUM

Tinactin®

Drug Facts

Active ingredient

Tolnaftate 1%

Purpose

Antifungal

Uses

- proven clinically effective in the treatment of most athlete's foot (tinea pedis) and ringworm (tinea corporis)
- helps prevent most athlete's foot with daily use
- for effective relief of itching, burning and cracking

Warnings

For external use only

Do not use on children under 2 years of age except under the advice and supervision of a doctor.

When using this product avoid contact with the eyes

Stop use and ask a doctor if

- irritation occurs
- there is no improvement within 4 weeks

Keep out of reach of children. If swallowed, get medical help or contact a Poison Control Center right away.

Directions

- wash affected area and dry thoroughly
- apply a thin layer over affected area twice daily (morning and night)
- supervise children in the use of this product
- for athlete's foot: pay special attention to spaces between the toes; wear well-fitting, ventilated shoes and change shoes and socks at least once daily
- use daily for 4 weeks; if condition persists longer, ask a doctor
- to prevent athlete's foot, apply once or twice daily (morning and/or night)
- this product is not effective on the scalp or nails

Other information

store between 20° to 25°C (68° to 77°F)

Inactive ingredients

ceteth-20, cetostearyl alcohol, chlorocresol, mineral oil, propylene glycol, purified water, sodium phosphate monobasic, white petrolatum

Questions?

1-866-360-3266

Distributed by
Bayer HealthCare LLC, Whippany, NJ, USA, 07981

PRINCIPAL DISPLAY PANEL - 15 g Tube Carton

TOUCH ACTIN'

Tinactin®
tolnaftate ANTIFUNGAL

CURES AND PREVENTS

MOST ATHLETE'S FOOT

Relieves:

- itching
- burning

CREAM

NET WT 15G (1/2 OZ)